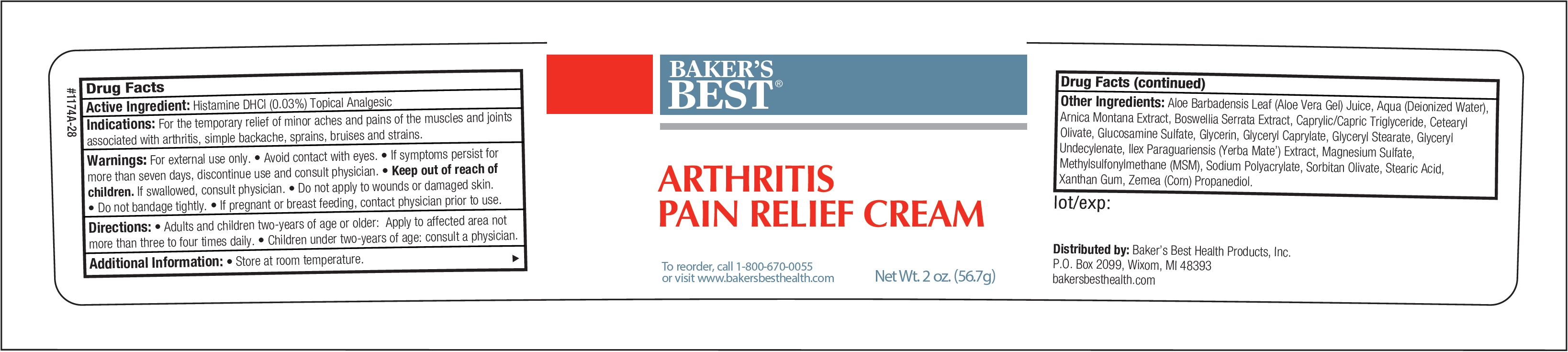 DRUG LABEL: Bakers Best Arthritis Pain Relief
NDC: 76102-030 | Form: CREAM
Manufacturer: Baker's Best Health Products, LLC
Category: otc | Type: HUMAN OTC DRUG LABEL
Date: 20260119

ACTIVE INGREDIENTS: HISTAMINE DIHYDROCHLORIDE 0.3 mg/1 g
INACTIVE INGREDIENTS: ALOE VERA LEAF; WATER; ARNICA MONTANA; INDIAN FRANKINCENSE; MEDIUM-CHAIN TRIGLYCERIDES; CETEARYL OLIVATE; GLUCOSAMINE SULFATE; GLYCERIN; GLYCERYL CAPRYLATE; GLYCERYL MONOSTEARATE; GLYCERYL 1-UNDECYLENATE; ILEX PARAGUARIENSIS LEAF; MAGNESIUM SULFATE, UNSPECIFIED FORM; DIMETHYL SULFONE; SORBITAN OLIVATE; STEARIC ACID; XANTHAN GUM; CORN

Baker's Best Arthritis Pain Relief Cream

Active Ingredient:

Histamine DHCl (0.03%)

PURPOSE

Topical Analgesic

Indications:

For the temporary relief of minor aches and pains of the muscles and joints associated with arthritis, simple backache, sprains, bruises and strains.

Warnings:

For external use only. • Avoid contact with eyes. • If symptoms persist for more than seven days, discontinue use and consult physician.

Keep out of reach of children.

If swallowed, consult physician.

Do not apply

- to wounds or damaged skin.
- Do not bandage tightly.

If pregnant or breast feeding,

contact physician prior to use.

Directions:

• Adults and children two-years of age or older: Apply to affected area not more than three to four times daily. • Children under two-years of age: consult a physician.

Additional Information:

• Store at room temperature.

Other Ingredients:

Aloe Barbadensis Leaf (Aloe Vera Gel) Juice, Aqua (Deionized Water), Arnica Montana Extract, Boswellia Serrata Extract, Caprylic/Capric Triglyceride, Cetearyl Olivate, Glucosamine Sulfate, Glycerin, Glyceryl Caprylate, Glyceryl Stearate, Glyceryl Undecylenate, Ilex Paraguariensis (Yerba Mate’) Extract, Magnesium Sulfate, Methylsulfonylmethane (MSM), Sodium Polyacrylate, Sorbitan Olivate, Stearic Acid, Xanthan Gum, Zemea (Corn) Propanediol.